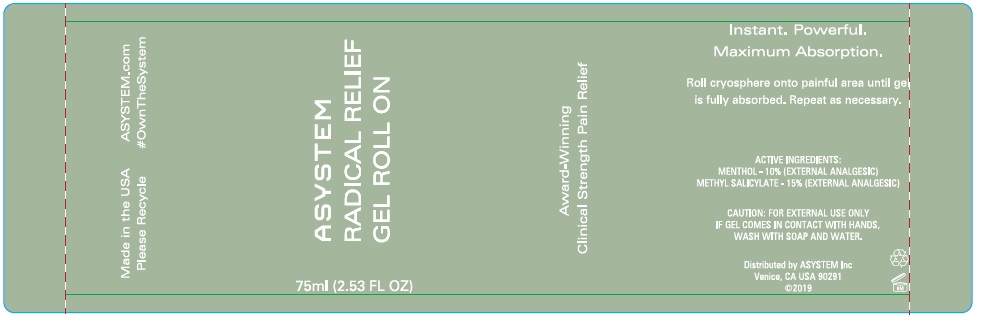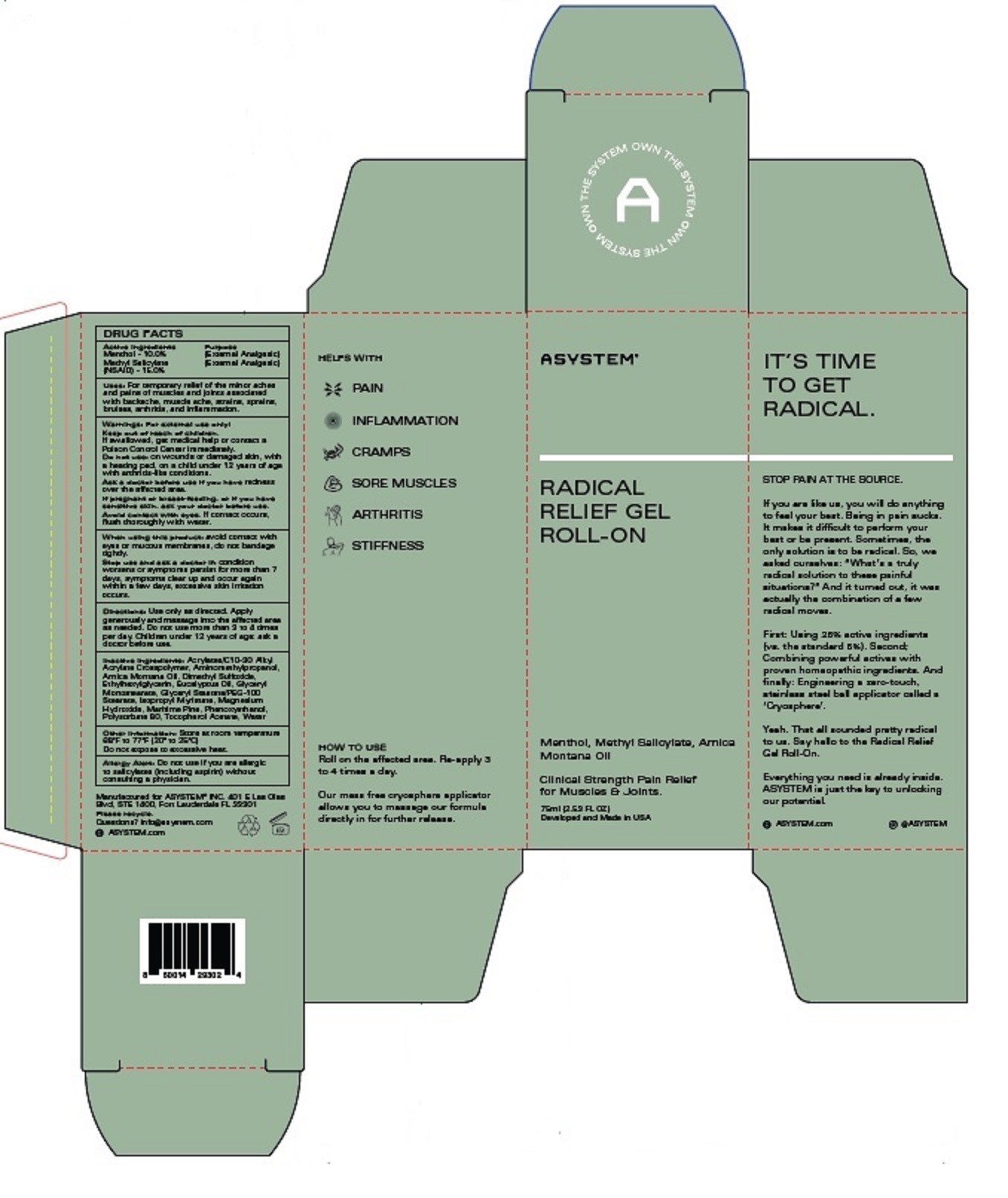 DRUG LABEL: ASYSTEM Radical Relief Gel Roll-On
NDC: 52261-4902 | Form: GEL
Manufacturer: Cosco International, Inc.
Category: otc | Type: HUMAN OTC DRUG LABEL
Date: 20260227

ACTIVE INGREDIENTS: MENTHOL 0.10 kg/1 kg; METHYL SALICYLATE 0.15 kg/1 kg
INACTIVE INGREDIENTS: WATER; CARBOMER INTERPOLYMER TYPE A (ALLYL SUCROSE CROSSLINKED); MARITIME PINE; DIMETHYL SULFOXIDE; ISOPROPYL MYRISTATE; GLYCERYL MONOSTEARATE; POLYSORBATE 80; ARNICA MONTANA FLOWER; .ALPHA.-TOCOPHEROL ACETATE, DL-; GLYCERYL STEARATE/PEG-100 STEARATE; EUCALYPTUS OIL; PHENOXYETHANOL; ETHYLHEXYLGLYCERIN; MAGNESIUM HYDROXIDE; AMINOMETHYLPROPANOL

ASYSTEM Radical Relief Gel Roll-On

DRUG FACTS

Menthol - 10% (External Analgesic)
Methyl Salicylate (NSAID) – 15% (External Analgesic)

PURPOSE

External Analgesic

Uses:

For temporary relief of the minor aches and pains of muscles and joints associated with backache, muscle ache, strains, sprains, bruises, cramps, arthritis, and inflammation.

Warnings:

For External Use Only

Keep out of reach of children.
If swallowed, get medical help or contact a Poison Control Center immediately.

Do not use: on wounds or damaged skin, with a heating pad, on a child under 12 years of age with arthritis-like conditions

Ask a doctor before use if you have redness over the affected area.

WHEN USING

Avoid contact with eyes. If contact occurs, flush throughly with water.

Directions:

Use only as directed. Apply generously and massage to affected area as needed. Do not use more than 3 to 4 times per day. Children under 12 years of age ; ask a doctor before use.

Inactive Ingredients:

Acrylates/C10-30 Alkyl Acrylate Crosspolymer, Aminomethylpropanol, Arnica Montana Oil, Dimethyl Sulfoxide, Ethylhexylglycerin, Eucalyptus Oil, Glyceryl Monostearate, Glyceryl Stearate/PEG-100 Stearate, Isopropyl Myristate, Magnesium Hydroxide, Maritime Pine, Phenoxyethanol, Polysorbate 80, Tocopherol Acetate, Water

OTHER SAFETY INFORMATION

Allery Alert: Do not use if you are allergic to salicylates (including aspritin) without consulting a physician.

Questions?

info@asystem.com